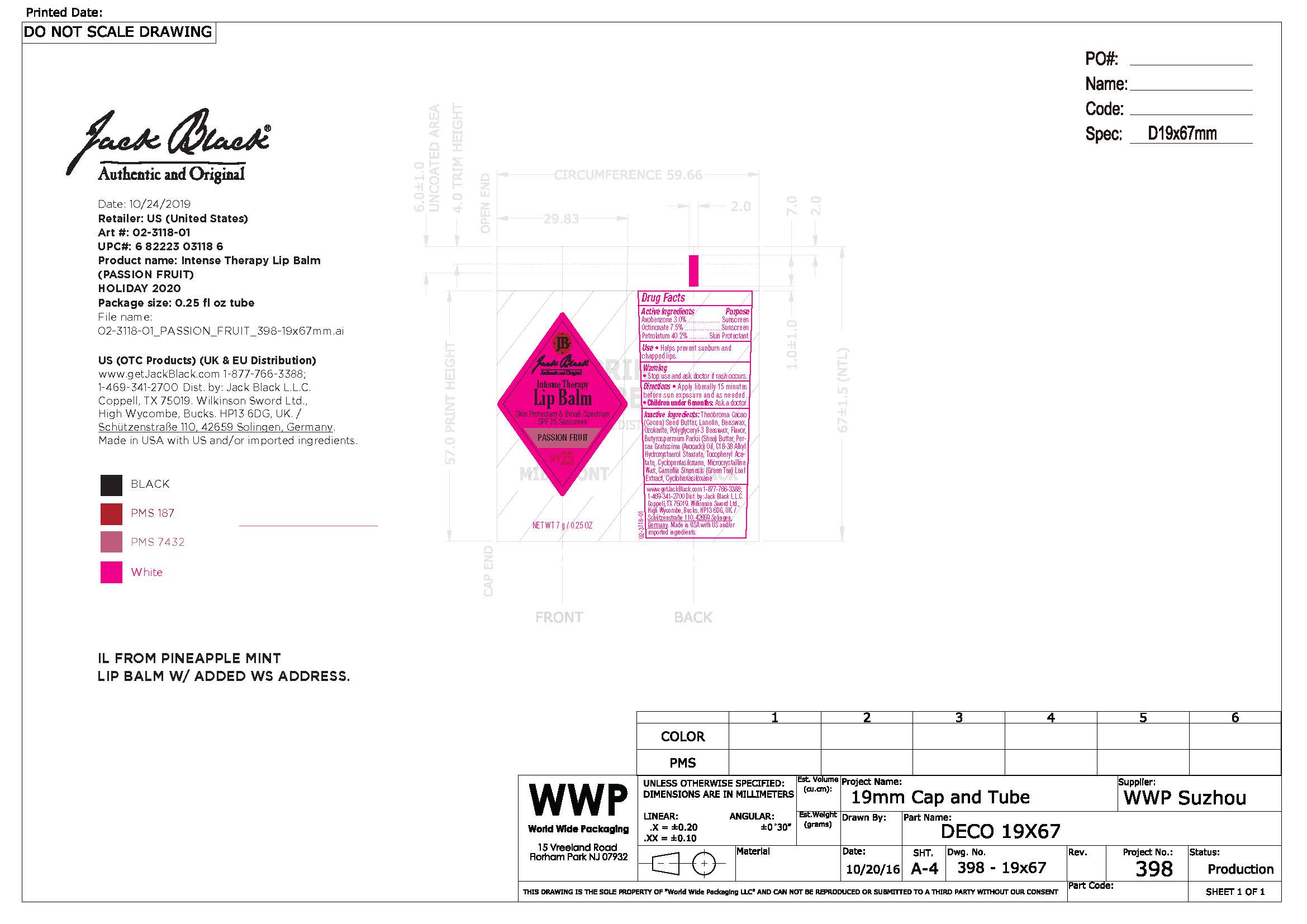 DRUG LABEL: Jack Black Intense Therapy Lip Balm Passion Fruit
NDC: 66738-065 | Form: OINTMENT
Manufacturer: Jack Black, LLC
Category: otc | Type: HUMAN OTC DRUG LABEL
Date: 20231108

ACTIVE INGREDIENTS: AVOBENZONE 30 g/100 g; OCTINOXATE 75 g/100 g; PETROLATUM 402 g/100 g
INACTIVE INGREDIENTS: COCOA BUTTER; LANOLIN; YELLOW WAX; SHEA BUTTER; CERESIN; AVOCADO OIL; .ALPHA.-TOCOPHEROL ACETATE; CYCLOMETHICONE 5; MICROCRYSTALLINE WAX; CAMELLIA SINENSIS WHOLE; CYCLOMETHICONE 6

Jack Black Intense Therapy Lip Balm Passion Fruit

Warnings

Stop use and ask doctor if rash occurs.

Keep out of reach of children

Active Ingredients

avobenzone 3.0% sunscreen

octinoxate 7.5% sunscreen

petrolatum 40.2% skin protectant

Uses

Helps prevent sunburn and chapped lips.

Uses

Helps prevent sunburn and chapped lips.

Directions

Apply liberally 15 minutes before sun exposure. Children under 6 months: ask a doctor.

Inactive Ingredients

theobroma cacao (coca) seed butter, lanolin, beeswax, ozokerite, polyglyceryl-3 beeswax, flavor, butyrospermum parkii (shea) butter, persea gratissima (avocado) oil, C18-38 alkyl hydroxystearol stearate, tocopheryl acetate, cyclopentasiloxane, microcrystalline wax, camellia sinenesis (green tea) leaf extract, cyclohexasiloxane

Questions

www.getjackblack.com

1-877-766-3388